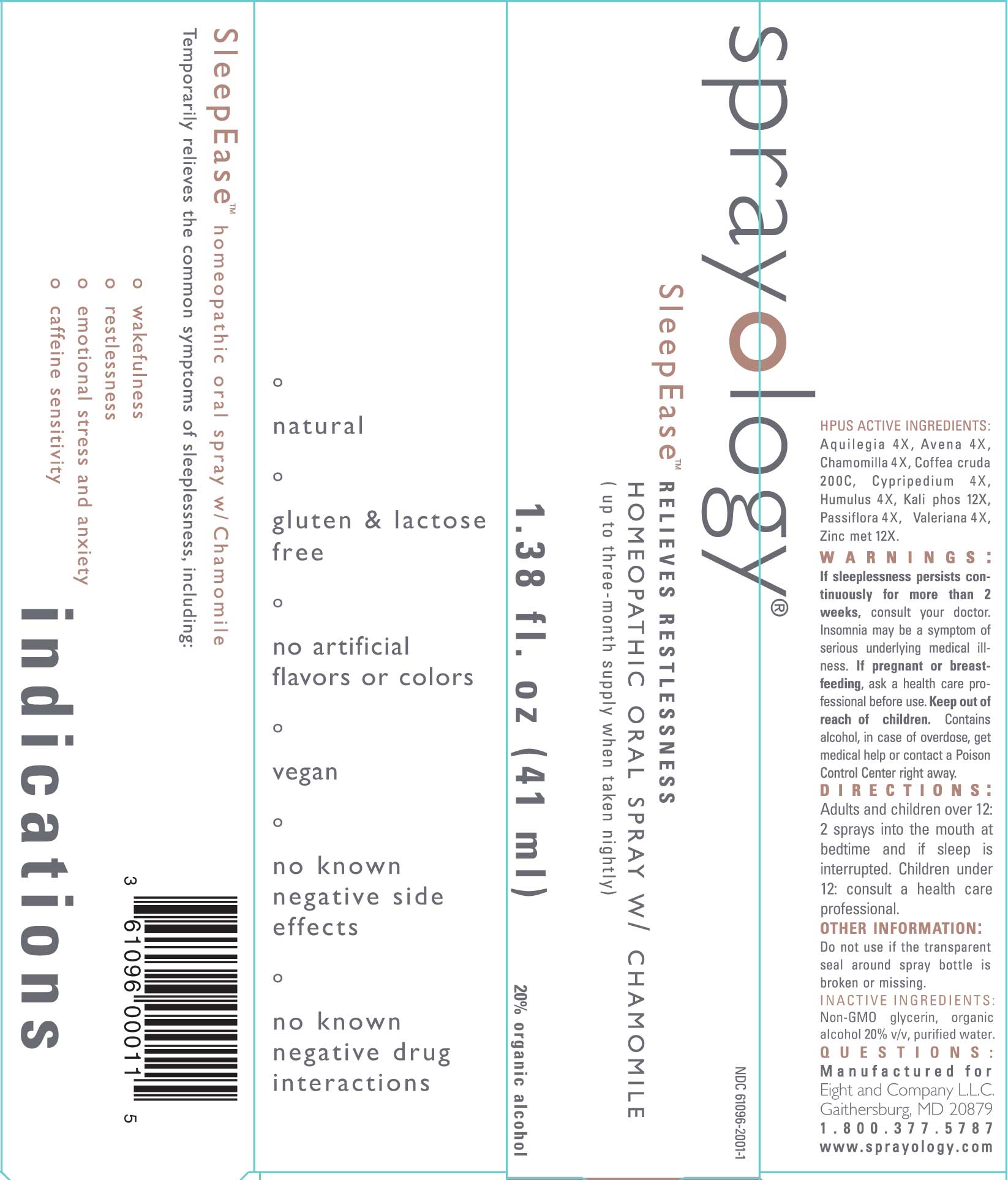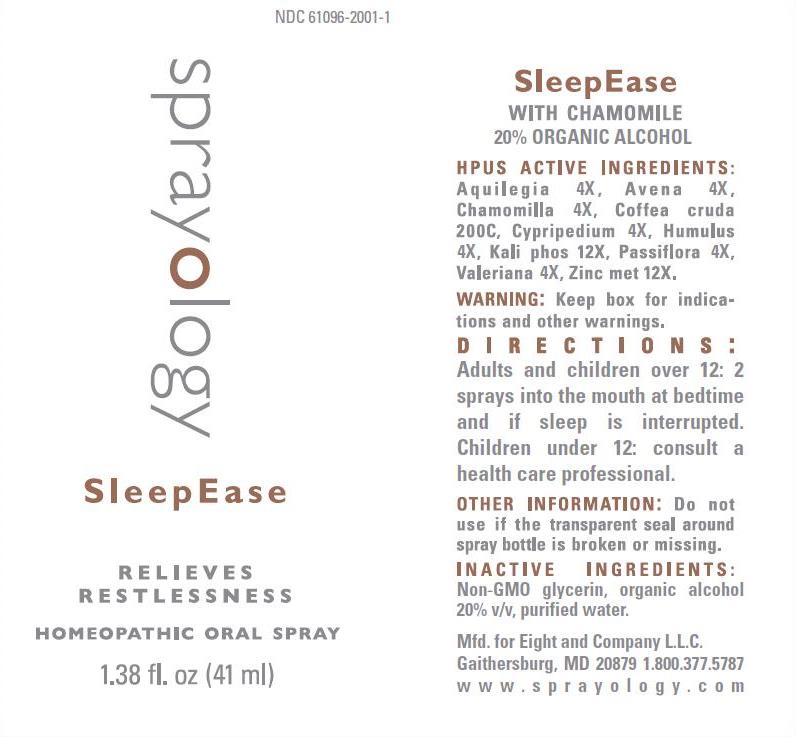 DRUG LABEL: SleepEase
NDC: 61096-2001 | Form: LIQUID
Manufacturer: Eight & Company L.L.C
Category: homeopathic | Type: HUMAN OTC DRUG LABEL
Date: 20251218

ACTIVE INGREDIENTS: AQUILEGIA VULGARIS 4 [hp_X]/41 mL; AVENA SATIVA FLOWERING TOP 4 [hp_X]/41 mL; MATRICARIA CHAMOMILLA WHOLE 4 [hp_X]/41 mL; ARABICA COFFEE BEAN 200 [hp_C]/41 mL; CYPRIPEDIUM PARVIFLORUM VAR. PUBESCENS ROOT 4 [hp_X]/41 mL; HOPS 4 [hp_X]/41 mL; DIBASIC POTASSIUM PHOSPHATE 12 [hp_X]/41 mL; PASSIFLORA INCARNATA FLOWERING TOP 4 [hp_X]/41 mL; VALERIAN 4 [hp_X]/41 mL; ZINC 12 [hp_X]/41 mL
INACTIVE INGREDIENTS: GLYCERIN; ALCOHOL; WATER

SleepEase

ACTIVE INGREDIENTS:

Aquilegia 4X, Avena 4X, Chamomilla 4X, Coffea cruda 200C, Cypripedium 4X, Humulus 4X, Kali phos 12X, Passiflora 4X, Valeriana 4X, Zinc met 12X.

WARNINGS:

If sleeplessness persists continuously for more than 2 weeks, consult your doctor. Insomnia may be a symptom of serious underlying medical illness. If pregnant or breast-feeding, ask a health care professional before use. Keep out of reach of children. Contains alcohol, in case of overdose, get medical help or contact a Poison Control Center right away.

KEEP OUT OF REACH OF CHILDREN:

Contains alcohol, in case of overdose, get medical help or contact a Poison Control Center right away.

INDICATIONS:

Temporarily relieves the common symptoms of sleeplessness, including:

º wakefulness

º restlessness

º emotional stress and anxiety

º caffeine sensitivity

DIRECTIONS:

Adults and children over 12: 2 sprays into the mouth at bedtime and if sleep is interrupted.Children Under 12: consult a health care professional.

OTHER INFORMATION:

Do not use if the transparent seal around spray bottle is broken or missing.

PURPOSE:

Temporarily relieves the common symptoms of sleeplessness, including:

° wakefulness

° restlessness

° emotional stress and anxiety

° caffeine sensitivity

° natural

° gluten free

° no artifical flavors or colors

° vegan

° no known negative side effects

° no known negative drug interactions

INACTIVE INGREDIENTS:

Non-GMO Glycerin, organic alcohol 20% v/v, purified water.

PACKAGE LABEL DISPLAY:

NDC 61096-2001-1

sprayology

SleepEase

RELIEVES

RESTLESSNESS

HOMEOPATHIC ORAL SPRAY

1.38 fl.oz (41 ml)